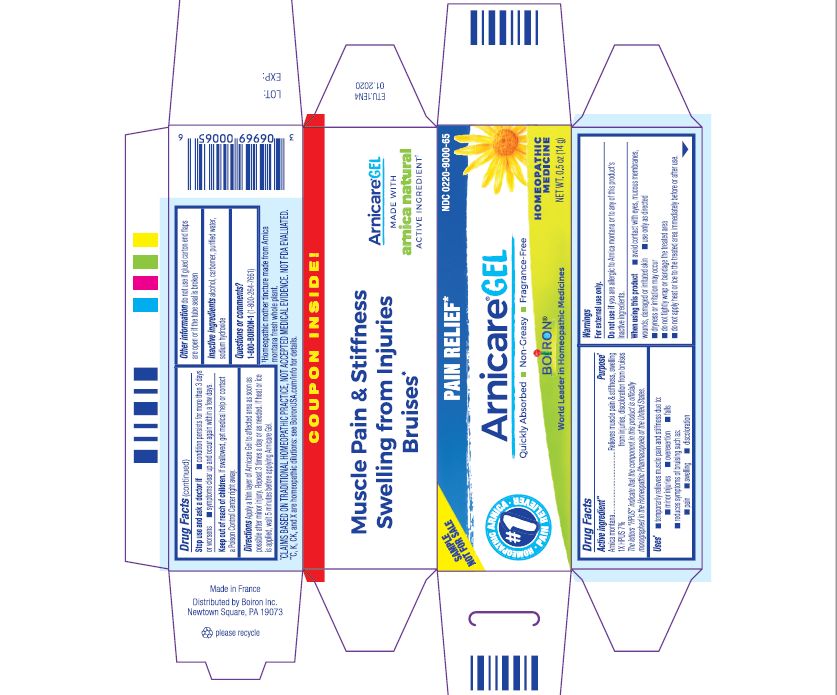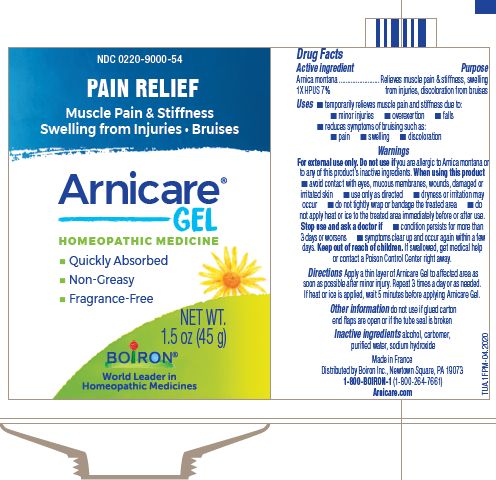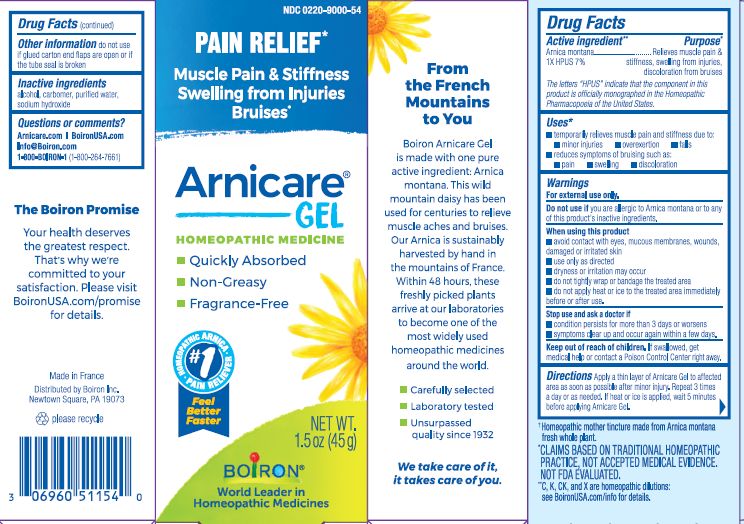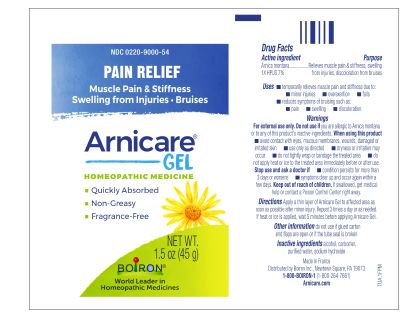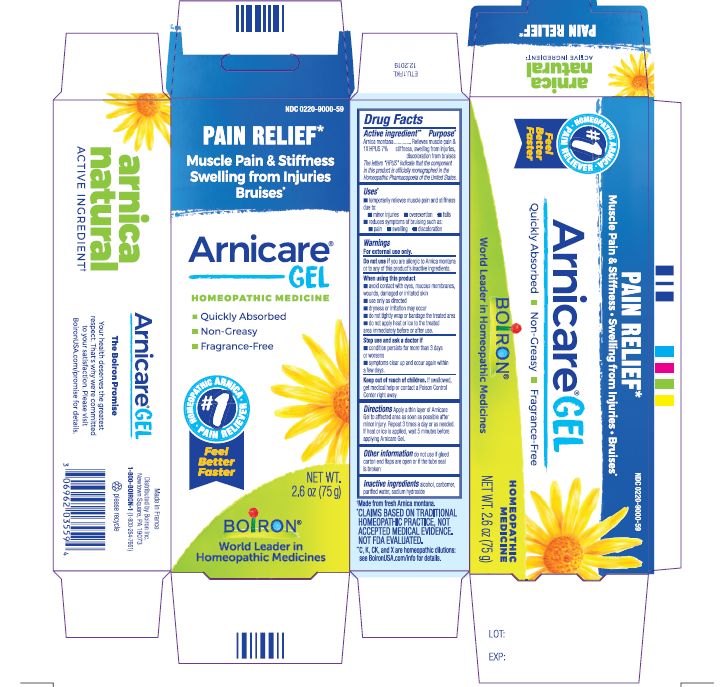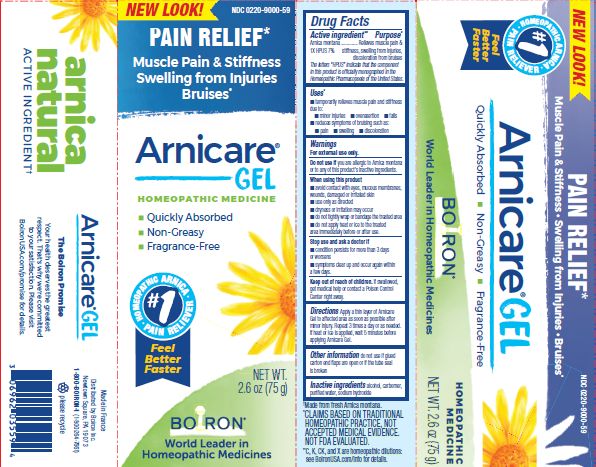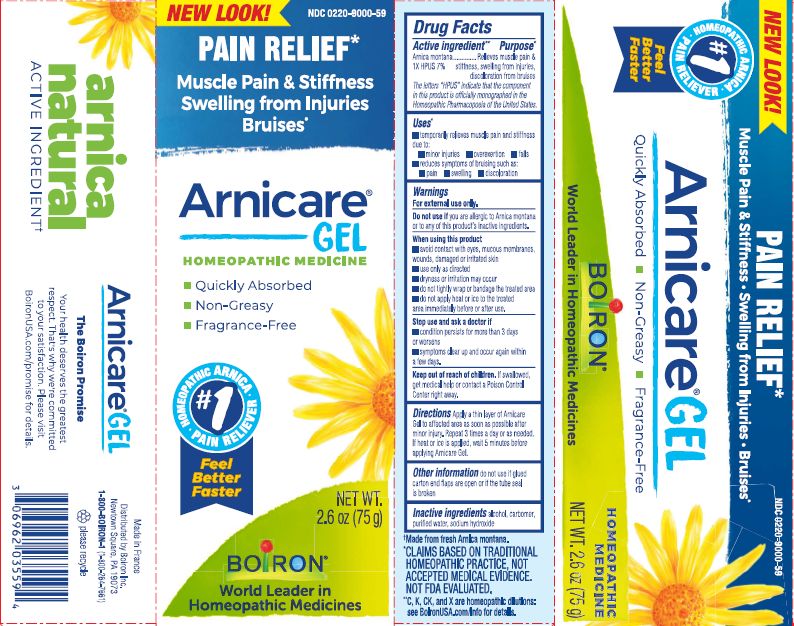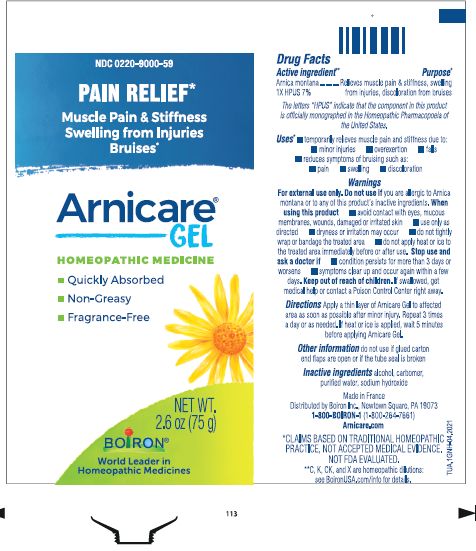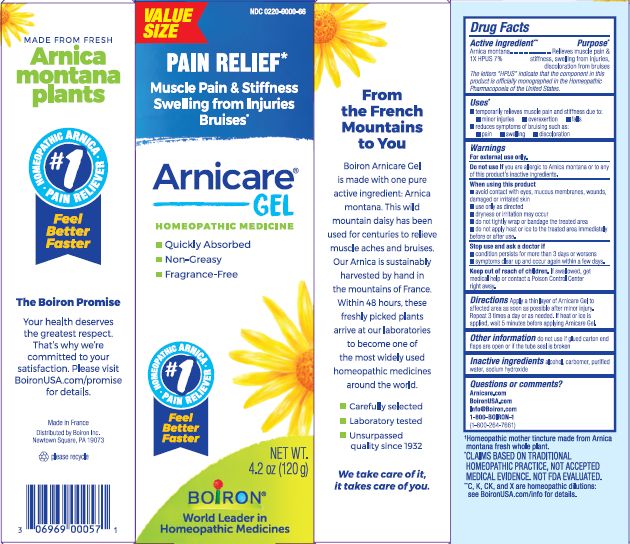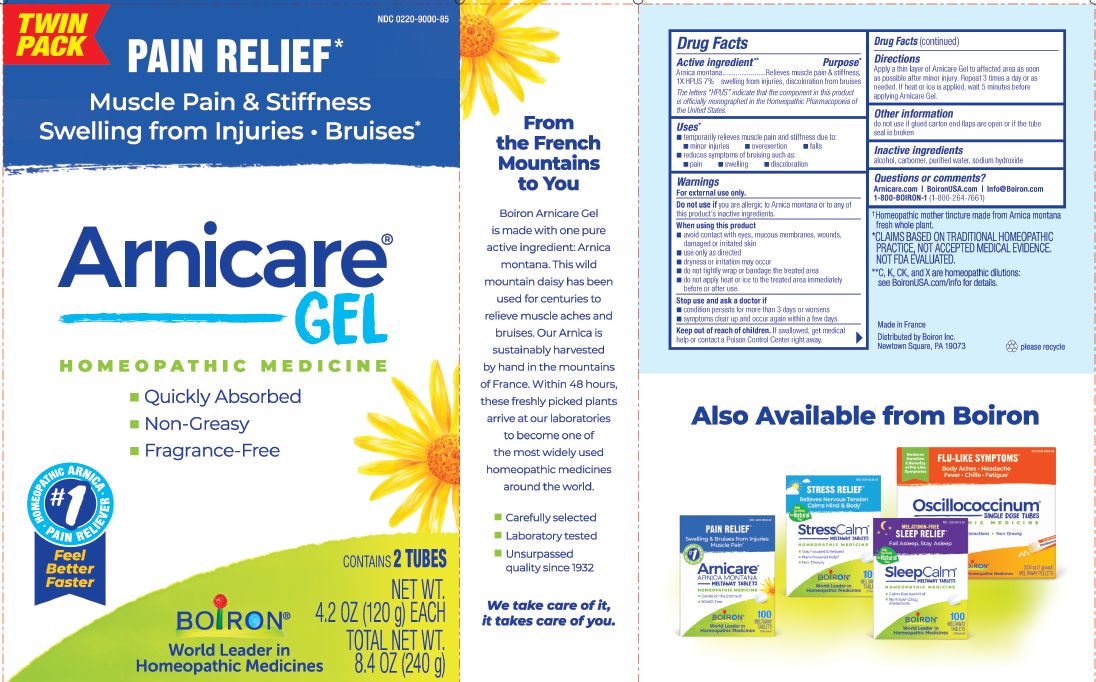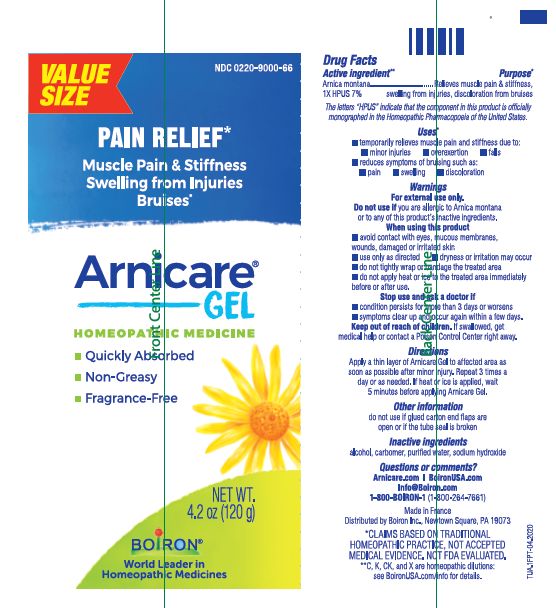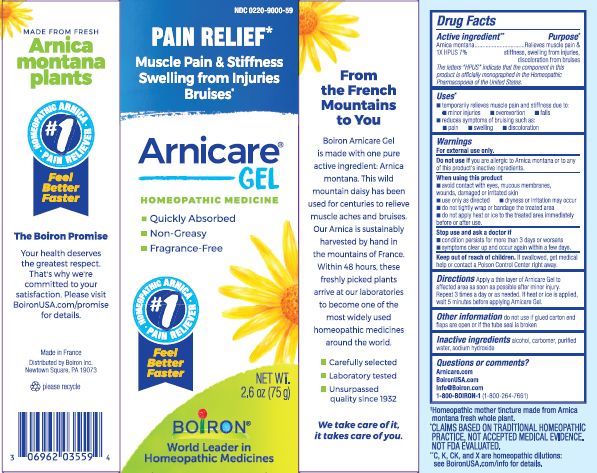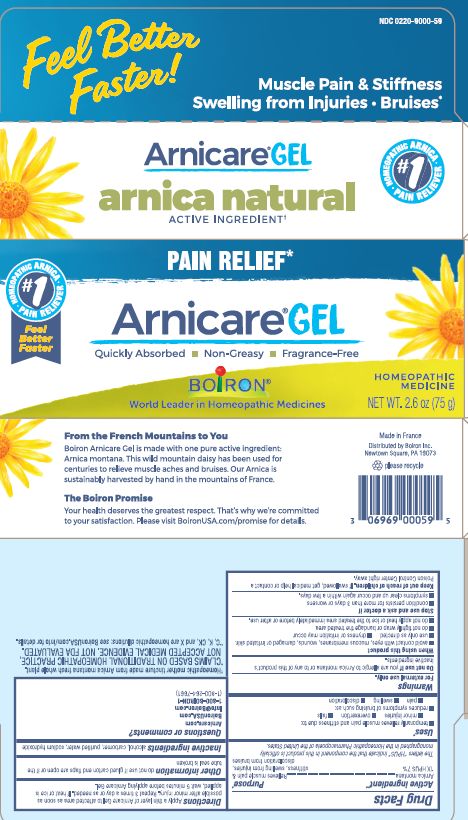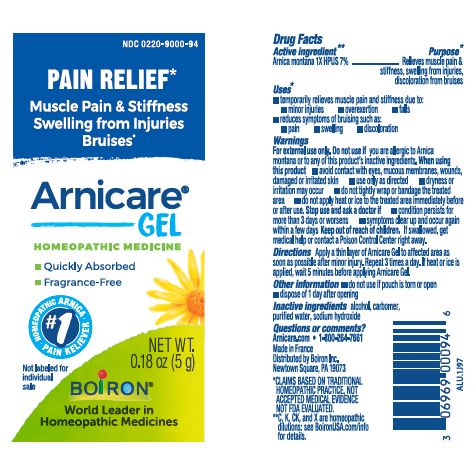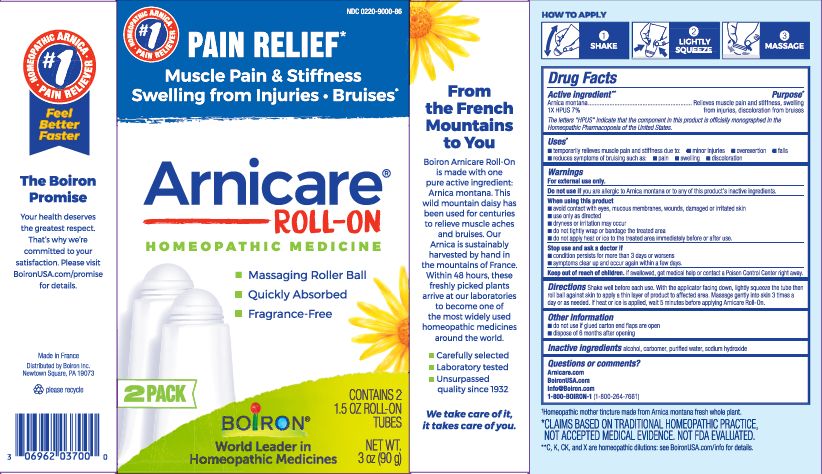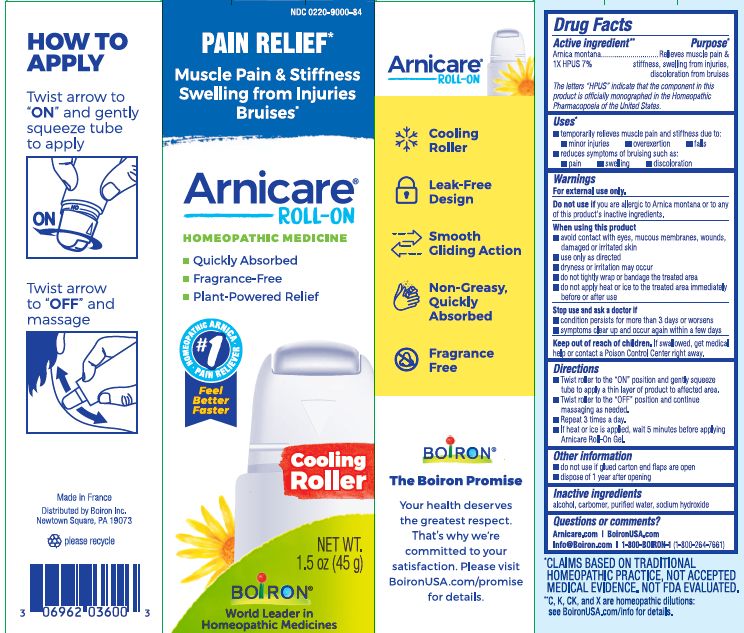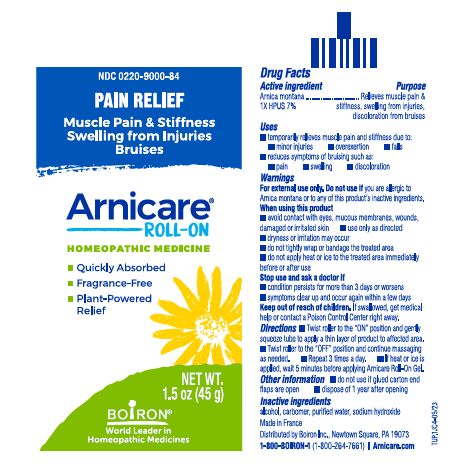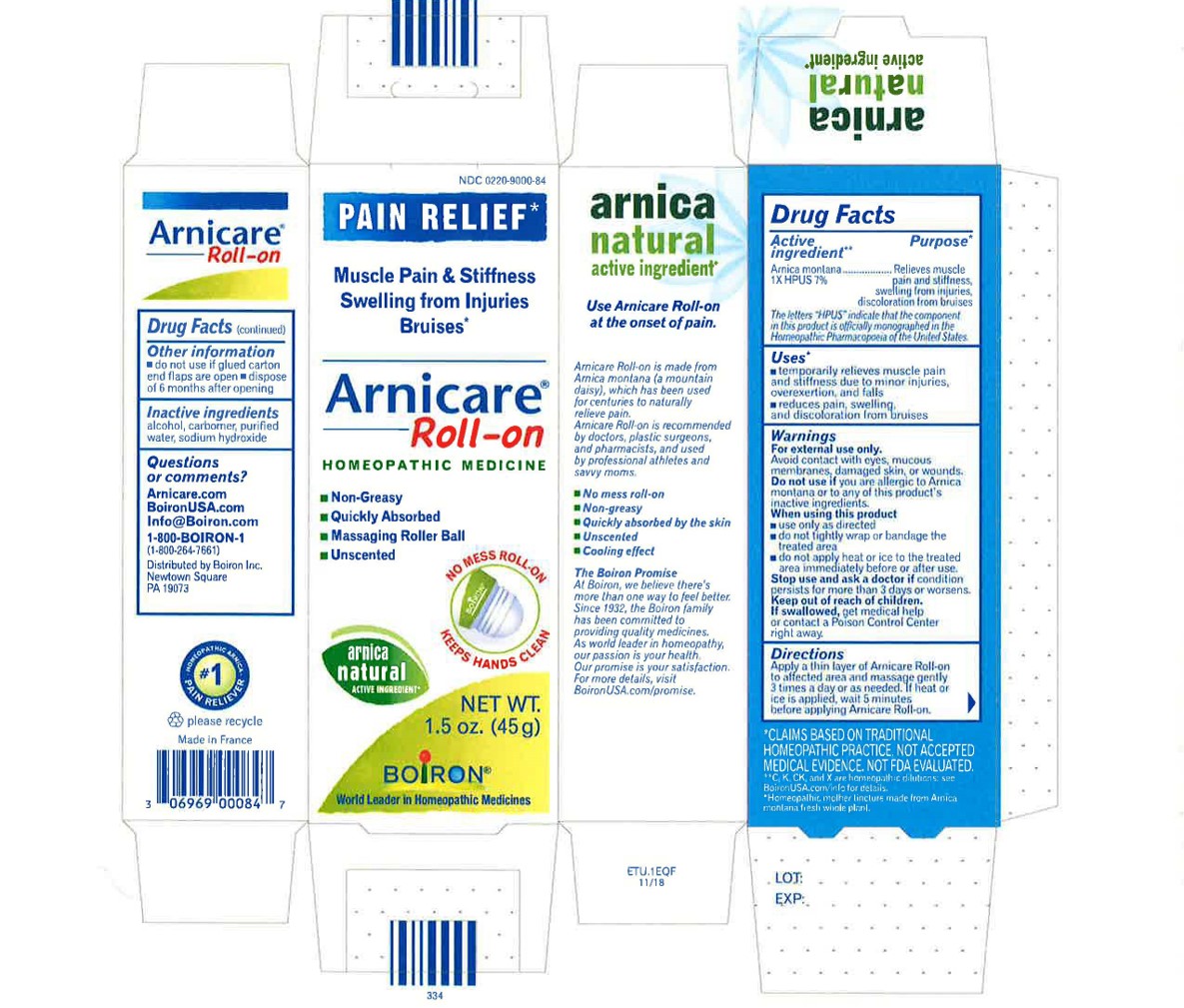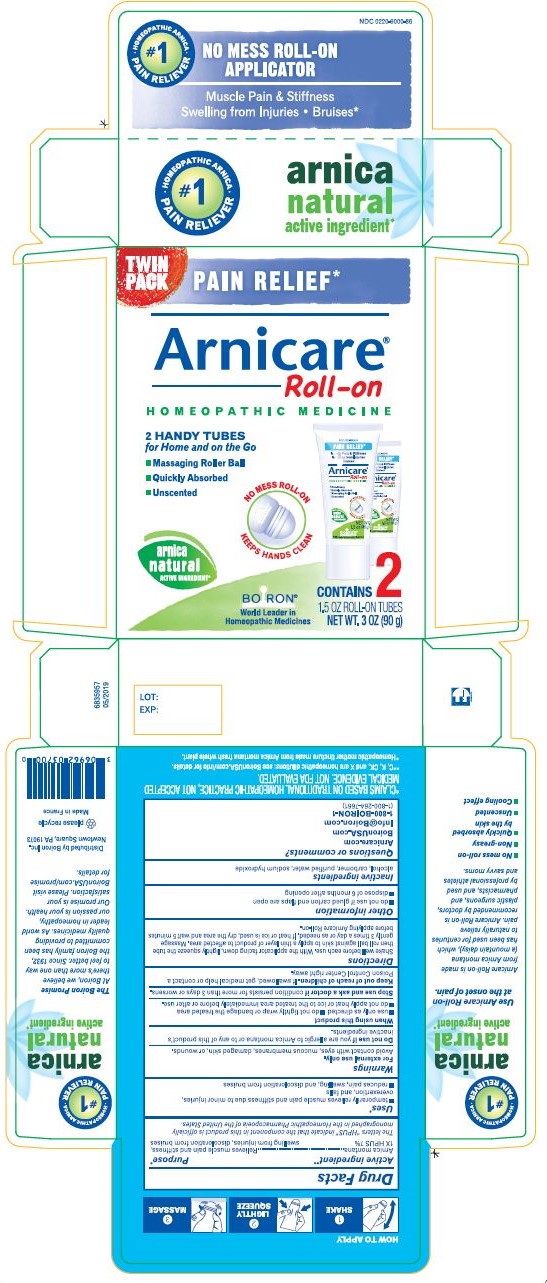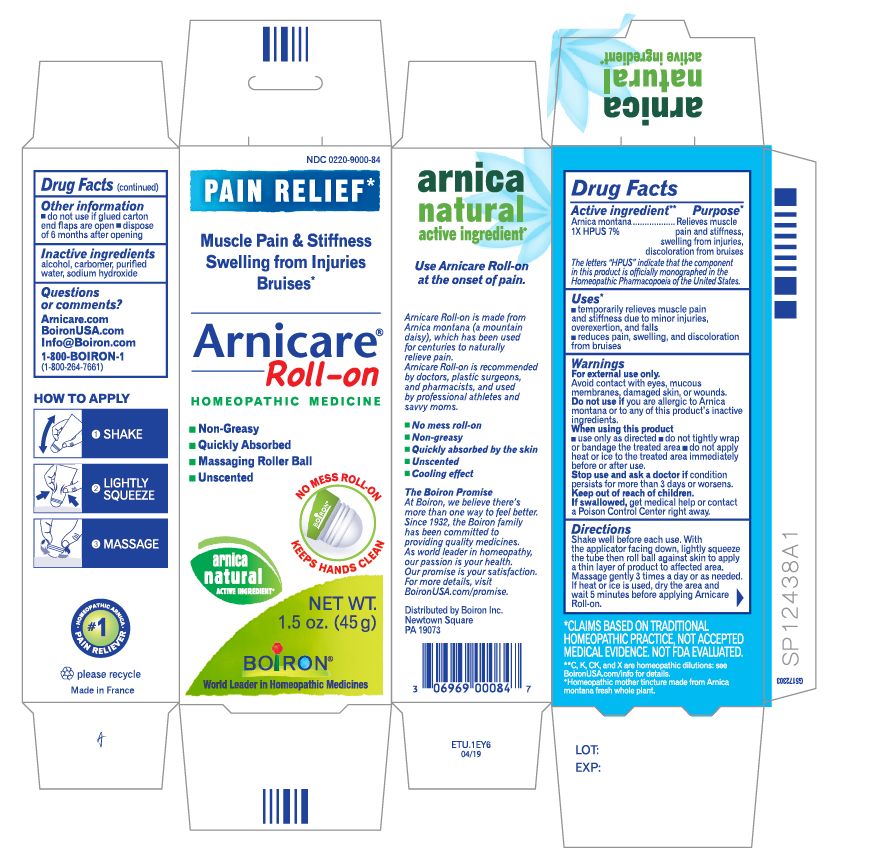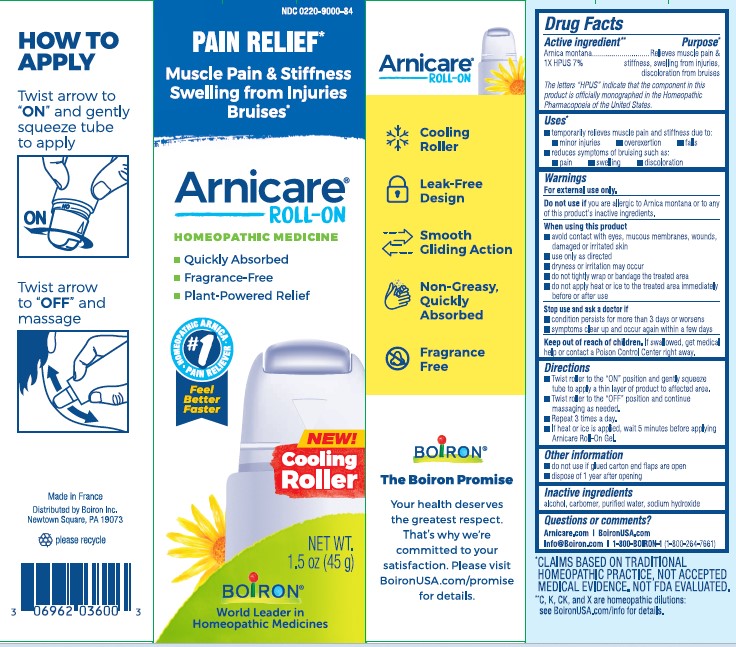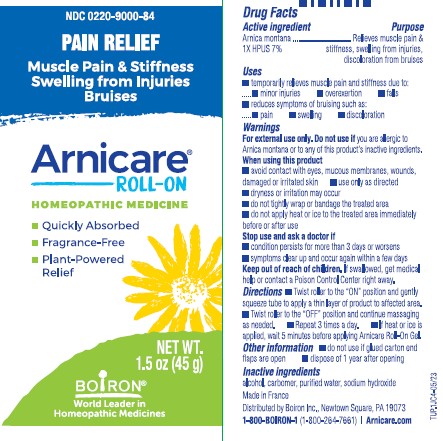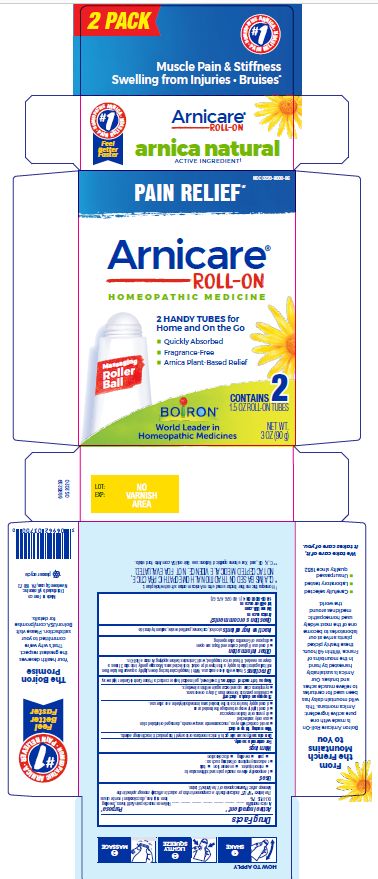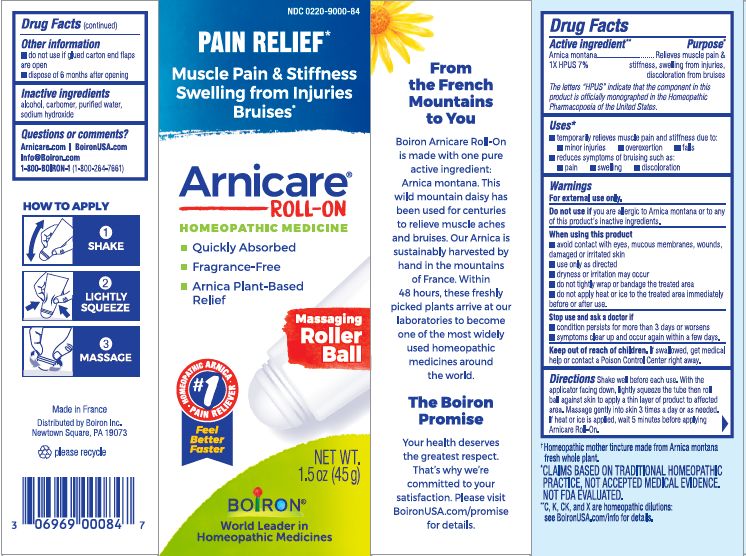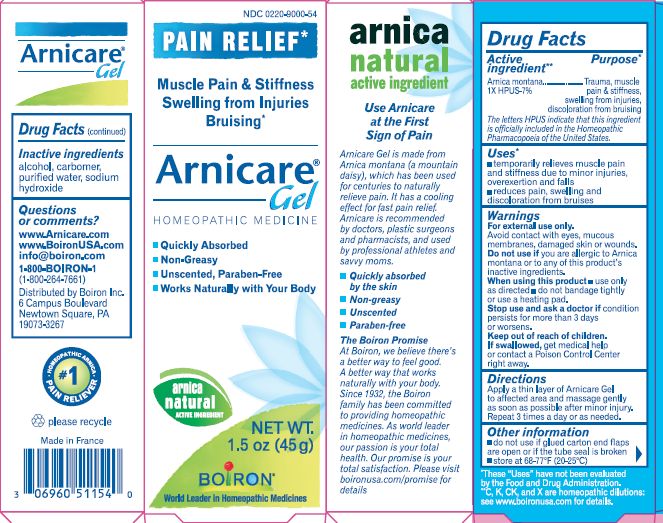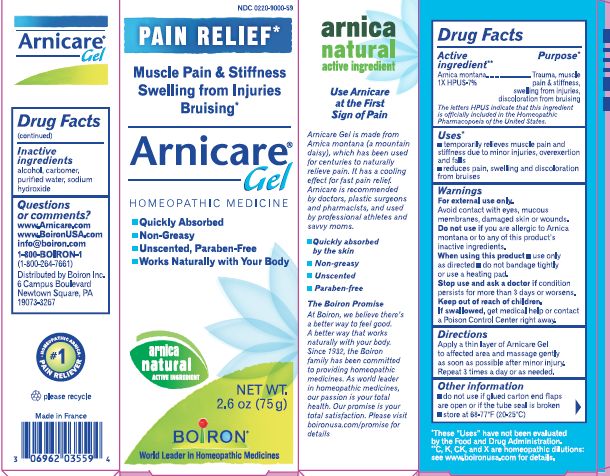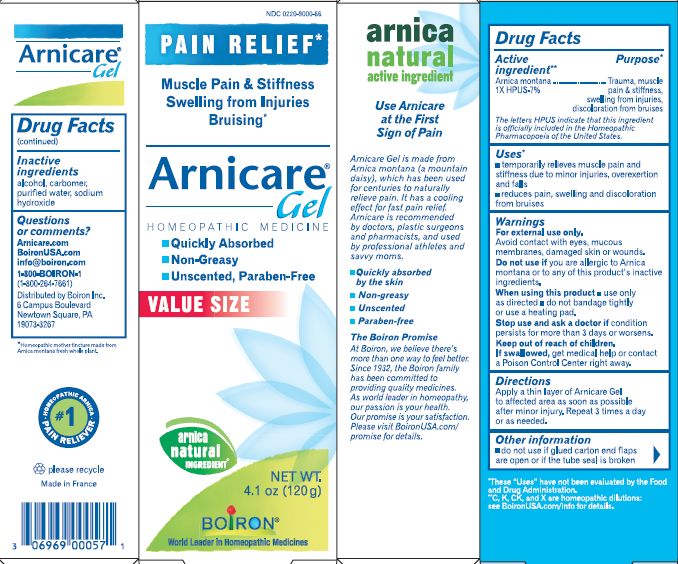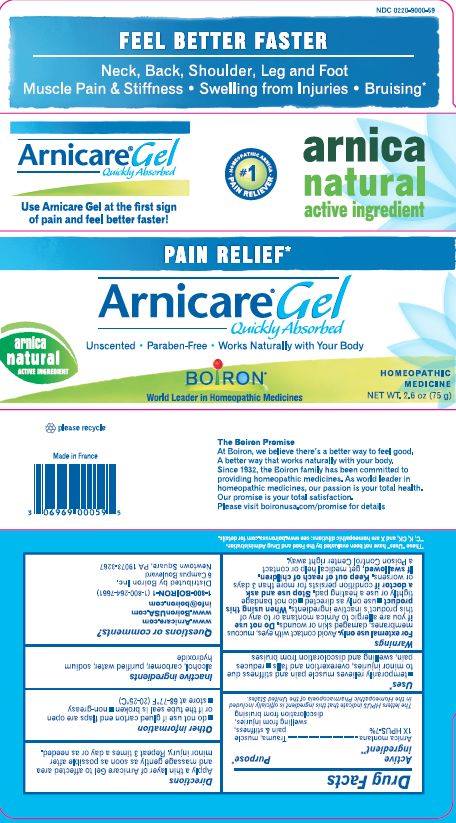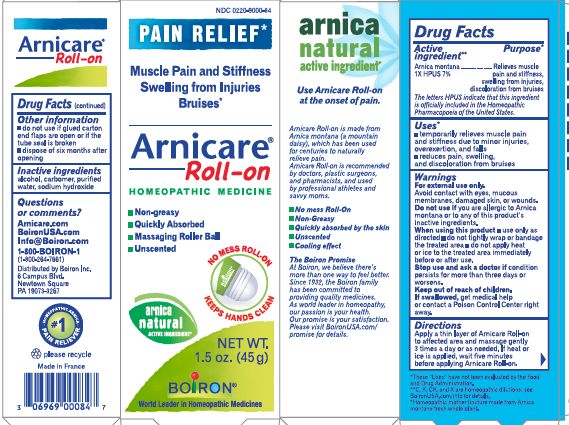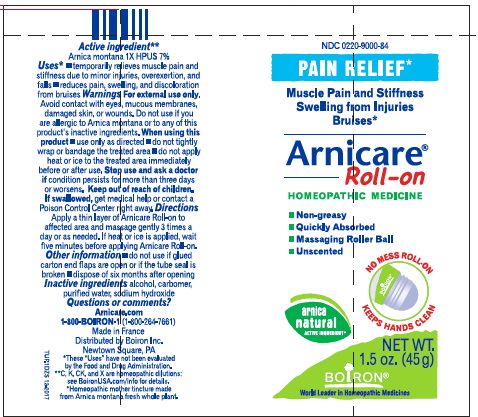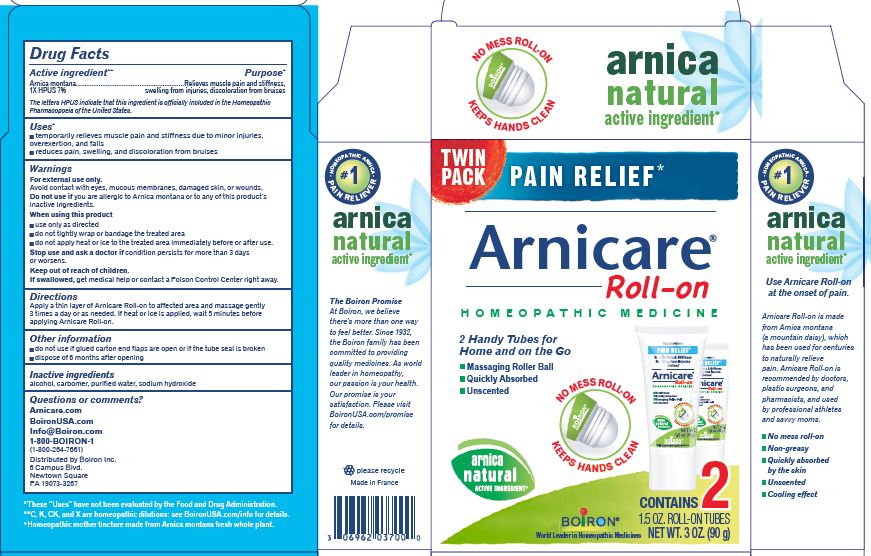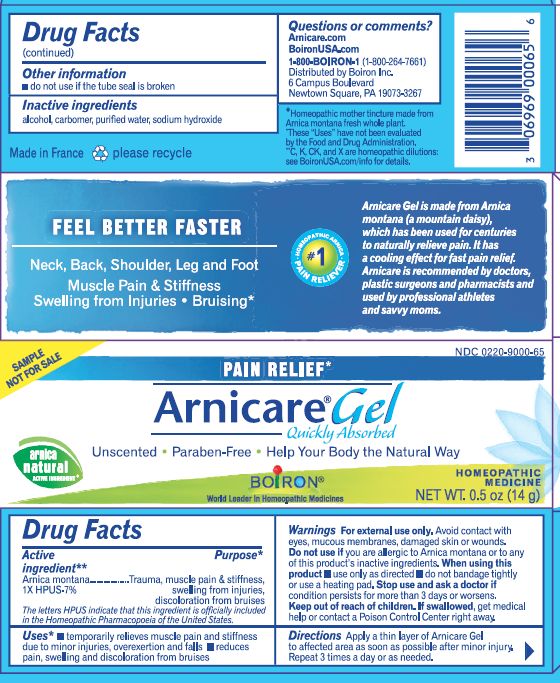 DRUG LABEL: Arnicare
NDC: 0220-9000 | Form: GEL
Manufacturer: Laboratoires Boiron
Category: homeopathic | Type: HUMAN OTC DRUG LABEL
Date: 20250721

ACTIVE INGREDIENTS: ARNICA MONTANA 1 [hp_X]/1 g
INACTIVE INGREDIENTS: ALCOHOL; WATER; SODIUM HYDROXIDE; CARBOMER HOMOPOLYMER TYPE C

Arnicare Gel

Active ingredient**

Arnica montana 1X HPUS 7%

The letters "HPUS" indicate that the component in this product is officially monographed in the Homeopathic Pharmacopoeia of the United States.

Purpose*

Arnica montana 1X HPUS 7% Relieves muscle pain & stiffness, swelling from injuries, discoloration from bruises

Uses*

temporarily relieves muscle pain and stiffness due to:

- minor injuries
- overexertion
- falls

reduces symptoms of bruising such as:

- pain
- swelling
- discoloration

Warnings

For external use only.

Do not use if you are allergic to Arnica montana or to any of this product's inactive ingredients.

When using this product

avoid contact with eyes, mucous membranes, wounds, damaged or irritated skin

use only as directed

dryness or irritation may occur

do not tightly wrap or bandage the treated area

do not apply heat or ice to treated area immediately before or after use.

Stop use and ask a doctor if

- condition persists for more than 3 days or worsens
- symptoms clear up and occur again within a few days.

Keep out of reach of children. If swallowed, get medical help or contact a Poison Control Center right away.

Directions

Apply a thin layer of Arnicare Gel to the affected area as soon as possible after minor injury. Repeat 3 times a day or as needed. If heat or ice is applied, wait 5 minutes before applying Arnicare Gel.A

Arnicare Gel Roll-On - Twist roller to the "ON" position and gently squeeze tube to apply a thin layer of product to affected area. Twist roller to the "OFF" position and continue massaging as needed. Repeat 3 times a day. If heat or ice is applied, wait 5 minutes before applying Arnicare Roll-on Gel.

INACTIVE INGREDIENT

Alcohol, carbomer, purified water, sodium hydroxide

Other information

do not use if glued carton end flaps are open or if the tube seal is broken

do not use if pouch is torn or open

Arnicare Gel 0.18 oz (5g)- dispose 1 day after opening

Arnicare Gel Roll-On (2023)- dispose of 1 year after opening

0.18 oz (5g)

0.5 oz (14g)

1.5 oz (45g)

2.6 oz (75g)

4.2 oz (120g)

3 oz (90g)

Pain Relief*

Muscle Pain & Stiffness Swelling from Injuries Bruises*

*CLAIMS BASED ON TRADITIONAL HOMEOPATHIC PRACTICE, NOT ACCEPTED MEDICAL EVIDENCE. NOT FDA EVALUATED.

*C,K,CK, and X are homeopathic dilutions: see BoironUSA.com/info for details.

Questions, Comments?

Distributed by Boiron, Inc., Newtown Square, PA 19073

1-800-BOIRON-1 (1-800-264-7661)

BoironUSA.com

Arnicare.com

Info@Boiron.com

Made in France